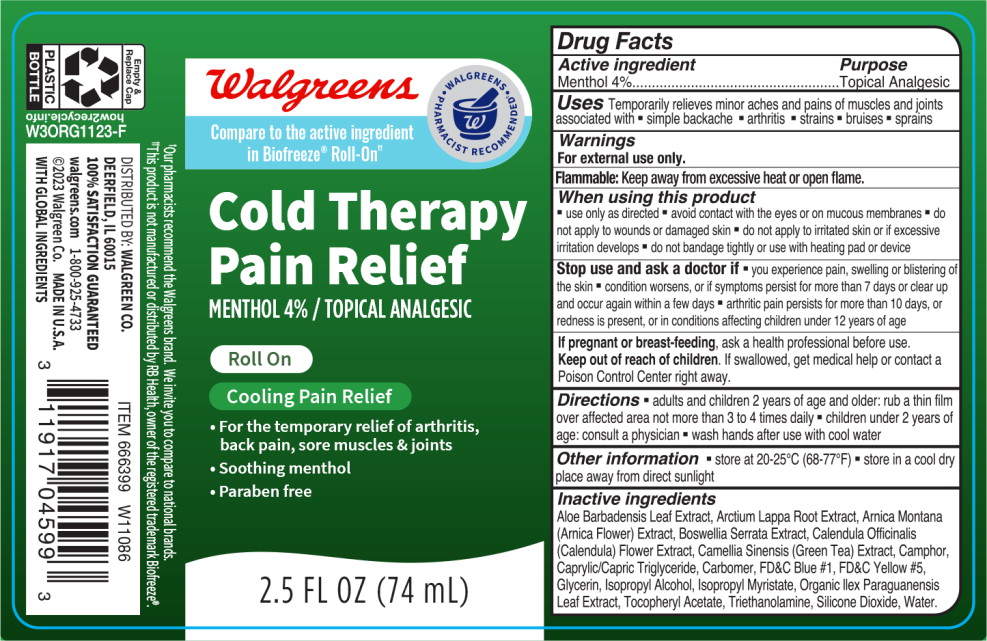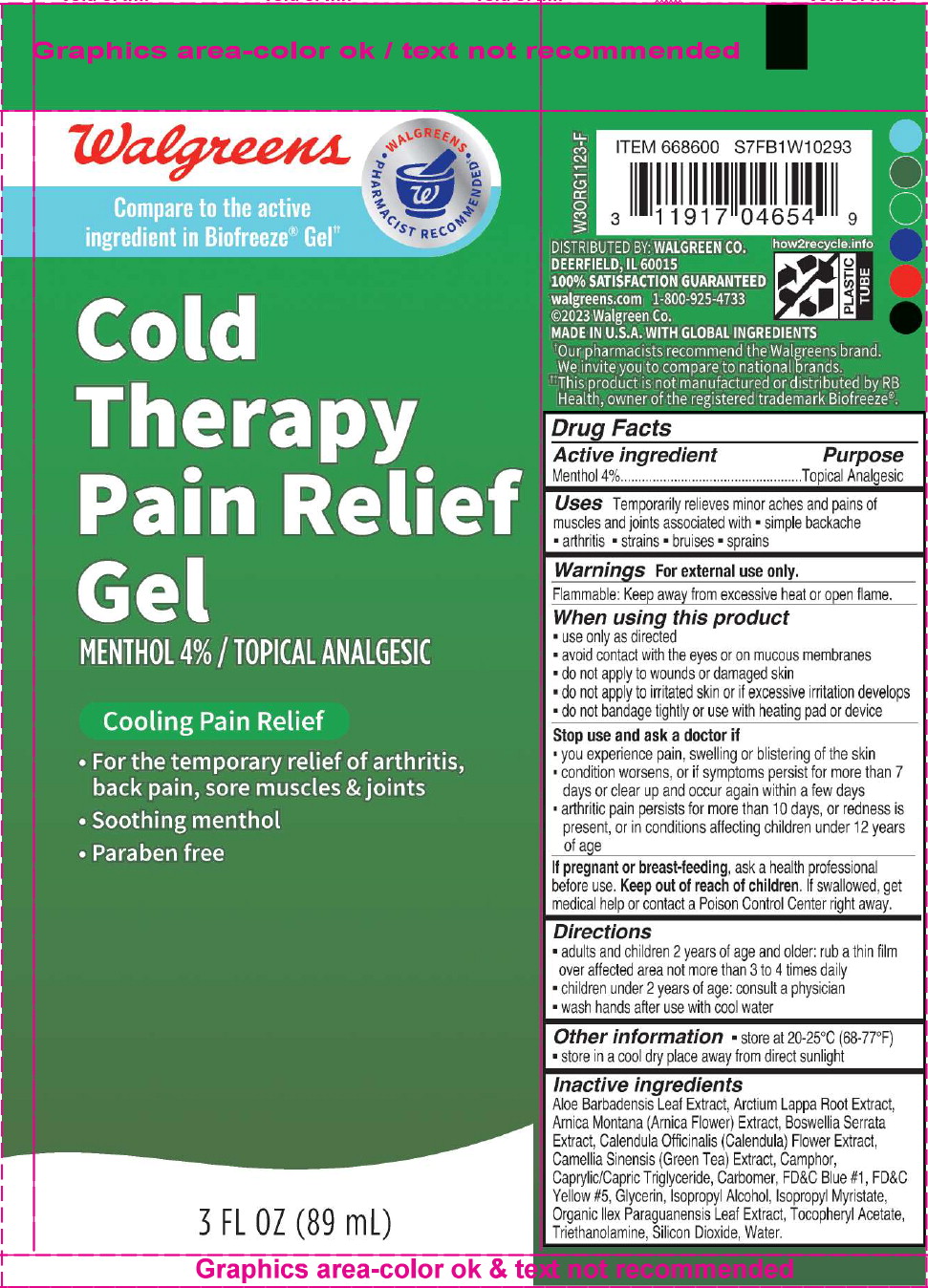 DRUG LABEL: Cold Therapy Pain Relief
NDC: 0363-0356 | Form: GEL
Manufacturer: Walgreen Co.
Category: otc | Type: HUMAN OTC DRUG LABEL
Date: 20240422

ACTIVE INGREDIENTS: MENTHOL, UNSPECIFIED FORM 36 mg/1 mL
INACTIVE INGREDIENTS: ALOE VERA LEAF; ARCTIUM LAPPA ROOT; ARNICA MONTANA FLOWER; INDIAN FRANKINCENSE; CALENDULA OFFICINALIS FLOWER; GREEN TEA LEAF; CAMPHOR (SYNTHETIC); CARBOMER HOMOPOLYMER TYPE C (ALLYL PENTAERYTHRITOL CROSSLINKED); FD&C BLUE NO. 1; FD&C YELLOW NO. 5; GLYCERIN; ISOPROPYL ALCOHOL; ISOPROPYL MYRISTATE; ILEX PARAGUARIENSIS LEAF; SILICON DIOXIDE; .ALPHA.-TOCOPHEROL; TROLAMINE; WATER

Drug Facts

Active ingredient

Menthol 4%

Purpose

Topical Analgesic

Uses

Temporarily relieves minor aches and pains of muscles and joints associated with

- simple backache
- arthritis
- strains
- bruises
- sprains

Warnings

For external use only.

Flammable: Keep away from excessive heat or open flame.

When using this product

- use only as directed
- avoid contact with the eyes or on mucous membranes
- do not apply to wounds or damaged skin
- do not apply to irritated skin or if excessive irritation develops
- do not bandage tightly or use with heating pad or device

Stop use and ask a doctor if

- you experience pain, swelling or blistering oi the skin
- condition worsens, or if symptoms persist for more than 7 days or clear up and occur again within a few days
- arthritic pain persists for more than 10 days, or redness is present, or in conditions affecting children under 12 years of age

PREGNANCY OR BREAST FEEDING

If pregnant or breast-feeding, ask a health professional before use.

Keep out of reach of children. If swallowed, get medical help or contact a Poison Control Center right away.

Directions

- adults and children 2 years of age and older: rub a thin film over affected area not more than 3 to 4 times daily
- children under 2 years of age: consult a physician
- wash hands after use with cool water

Other information

- store at 20-25°C (68-77°F)
- store in a cool dry place away from direct sunlight

Inactive ingredients

Aloe Barbadensis Leaf Extract, Arctium Lappa Root Extract, Arnica Montana (Arnica Flower) Extract, Boswellia Serrata Extract, Calendula Officinalis (Calendula) Flower Extract, Camellia Sinensis (Green Tea) Extract, Camphor, Caprylic/Capric Triglyceride, Carbomer, FD&C Blue #1, FD&C Yellow #5, Glycerin, Isopropyl Alcohol, Isopropyl Myristate, Organic Ilex Paraguanensis Leaf Extract, Tocopheryl Acetate, Triethanolamine, Silicone Dioxide, Water.

Principal Display Panel – 74 mL Bottle Label

Walgreens

Compare to the active ingredient
in Biofreeze® Roll-On††

WALGREENS PHARMACIST RECOMMENDED

Cold Therapy
Pain Relief

MENTHOL 4% / TOPICAL ANALGESIC

Roll On

Cooling Pain Relief

- For the temporary relief of arthritis,
  back pain, sore muscles & joints
- Soothing menthol
- Paraben free

2.5 FL OZ (74 ml)

Principal Display Panel – 89 mL Tube Label

Walgreens

Compare to the active
ingredient in Biofreeze® Gel††

WALGREENS PHARMACIST RECOMMENDED

Cold
Therapy
Pain Relief
Gel

MENTHOL 4% / TOPICAL ANALGESIC

Cooling Pain Relief

- For the temporary relief of arthritis,
  back pain, sore muscles & joints
- Soothing menthol
- Paraben free

3 FL OZ (89 ml)